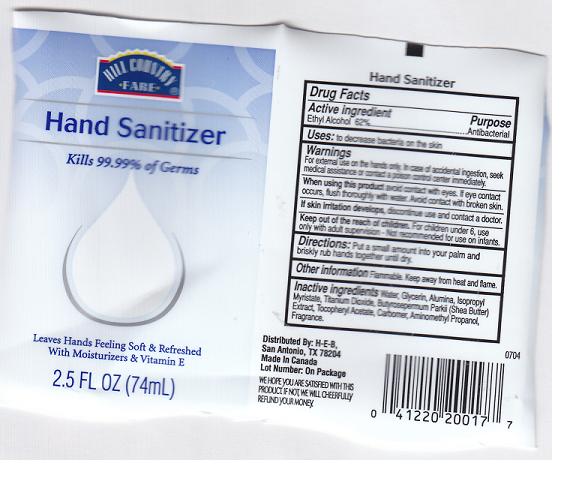 DRUG LABEL: HAND SANITIZER
NDC: 37808-238 | Form: GEL
Manufacturer: HEB
Category: otc | Type: HUMAN OTC DRUG LABEL
Date: 20110203

ACTIVE INGREDIENTS: ALCOHOL 62 mL/100 mL
INACTIVE INGREDIENTS: WATER; GLYCERIN; ALUMINUM OXIDE; ISOPROPYL MYRISTATE; TITANIUM DIOXIDE; SHEANUT OIL; .ALPHA.-TOCOPHEROL ACETATE, D-; CARBOMER 934; AMINOMETHYLPROPANOL

DRUG FACTS

ACTIVE INGREDIENT

ETHYL ALCOHOL 62%

PURPOSE

ANTIBACTERIAL

USES:

TO DECREASE BACTERIA ON THE SKIN.

WARNINGS

FOR EXTERNAL USE ON THE HANDS ONLY. IN CASE OF ACCIDENTAL INGESTION, SEEK MEDICAL ASSISTANCE OR CONTACT A POISON CONTROL CENTER IMMEDIATELY.

WHEN USING THIS PRODUCT

AVOID CONTACT WITH EYES. IF EYE CONTACT OCCURS, FLUSH THOROUGHLY WITH WATER. AVOID CONTACT WITH BROKEN SKIN.

IF SKIN IRRITATION DEVELOPS,

DISCONTINUE USE AND CONTACT A DOCTOR.

KEEP OUT OF REACH OF CHILDREN

FOR CHILDREN UNDER 6, USE ONLY WITH ADULT SUPERVISION. NOT RECOMMENDED FOR USE ON INFANTS.

DIRECTIONS:

PUT A SMALL AMOUNT IN YOUR PALM AND BRISKLY RUB HANDS TOGETHER UNTIL DRY.

OTHER INFORMATION

FLAMMABLE. KEEP AWAY FROM HEAT AND FLAME.

INACTIVE INGREDIENTS

WATER, GLYCERIN, ALUMINA, ISOPROPYL MYRISTATE, TITANIUM DIOXIDE, BUTYROSPERMUM PARKII (SHEA BUTTER) EXRACT, TOCOPHERYL ACETATE, CARBOMER, AMINOMETHYL PROPANOL, FRAGRANCE.